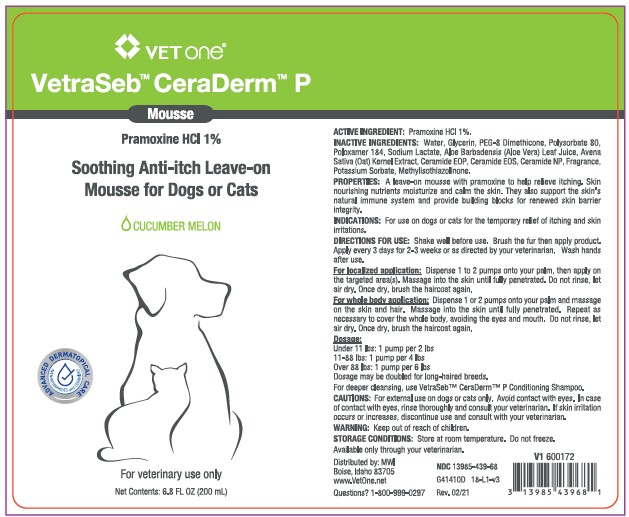 DRUG LABEL: VetraSeb CeraDerm
NDC: 13985-439 | Form: LIQUID
Manufacturer: MWI/VETONE
Category: animal | Type: OTC ANIMAL DRUG LABEL
Date: 20210420

ACTIVE INGREDIENTS: PRAMOXINE HYDROCHLORIDE 10 mg/1 mL
INACTIVE INGREDIENTS: WATER; GLYCERIN; PEG-8 DIMETHICONE; POLYSORBATE 80; POLOXAMER 184; ALOE VERA LEAF; AVENANTHRAMIDES; CERAMIDE 1; CERAMIDE EOS; CERAMIDE NP; POTASSIUM SORBATE; METHYLISOTHIAZOLINONE

DESCRIPTION

VetraSeb™ CeraDerm™ P

Soothing Anti-itch Leave-on Mousse for Dogs or Cats

CUCUMBER MELON

For veterinary use only

ACTIVE INGREDIENTS: Pramoxine HCl 1%.

INACTIVE INGREDIENTS: Water, Glycerin, PEG-8 Dimethicone, Polysorbate 80, Poloxamer 184, Sodium Lactate, Aloe Barbadensis (Aloe) Leaf Juice, Avena Sativa (Oat) Kernel Extract, Ceramide EOP, Ceramide EOS, Ceramide NP, Fragrance, Potassium Sorbate, Methylisothiazolinone.

PROPERTIES: A leave-on mousse with pramoxine to help relieve itching. Skin nourishing nutrients moisturize and calm the skin. They also support the skin's natural immune system and provide building blocks for renewed skin barrier integrity.

INDICATIONS AND USAGE

INDICATIONS: For use on dogs or cats for the temporary relief of itching and skin irritations.

DIRECTIONS FOR USE: Shake well before use. Brush the fur then apply product. Apply every 3 days for 2-3 weeks or as directed by your veterinarian. Wash hands after use.

For localized application: Dispense 1 to 2 pumps onto your palm, then apply on the targeted area(s). Massage into the skin until fully penetrated. Do not rinse, let air dry. Once dry, brush the haircoat again.

For whole body application: Dispense 1 or 2 pumps onto your palm and massage on the skin and hair. Massage into the skin until fully penetrated. Repeat as necessary to cover the whole body, avoiding the eyes and mouth. Do not rinse, let air dry. Once dry, brush the haircoat again.

Dosage:

Under 11 lbs: 1 pump per 2 lbs

11-88 lbs: 1 pump per 4 lbs

Over 88 lbs: 1 pump per 6 lbs

Dosage may be doubled for long-haired dogs. For deeper cleansing, use VetraSeb™ CeraDerm™ P Conditioning Shampoo.

WARNINGS AND PRECAUTIONS

CAUTIONS: For external use on dogs or cats only. Avoid contact with eyes. In case of contact with eyes, rinse thoroughly and consult your veterinarian. If skin irritation occurs or increases, discontinue use and consult with your veterinarian.

WARNING: Keep out of reach of children.

STORAGE AND HANDLING

STORAGE CONDITIONS: Store at room temperature. Do not freeze.

Distributed by: MWI

Boise, Idaho 83705

www.VetOne.net

QUESTIONS? 1-800-999-0297

PRINCIPAL DISPLAY PANEL - 6.8 OUNCE (200 mL) Bottle

VETone®

VetraSeb™ CeraDerm™ P

Mousse

Pramoxine HCl 1%

Soothing Anti-itch Leave-on Mousse for Dogs or Cats

CUCUMBER MELON

For veterinary use only

Net Contents: 6.8 FL. OZ. (200 mL)